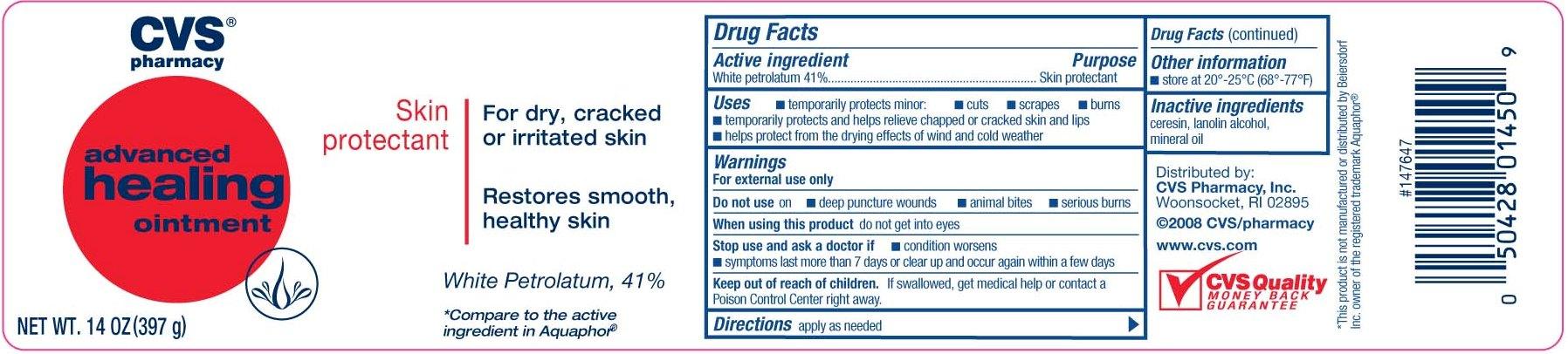 DRUG LABEL: CVS Advanced Healing
NDC: 59779-904 | Form: OINTMENT
Manufacturer: CVS
Category: otc | Type: HUMAN OTC DRUG LABEL
Date: 20120426

ACTIVE INGREDIENTS: PETROLATUM 410 mg/1 g
INACTIVE INGREDIENTS: LANOLIN ALCOHOLS; CERESIN; MINERAL OIL

drug facts

Active ingredient Purpose
White Petrolatum 41% .........................Skin protectant

Uses
Temporarily protects minor - cuts - scrapes - burns
Temporarily protects and helps relieve chapped or cracked skin or lips
Helps protect from the drying effects of wind and cold weather

Keep out of reach of children. If swallowed, get
medical help or contact a Poison Control Center right away.

Uses
Temporarily protects minor - cuts - scrapes - burns
Temporarily protects and helps relieve chapped or cracked skin or lips
Helps protect from the drying effects of wind and cold weather

Warnings
For external use only.
Do not use on - deep puncture wounds - animal bites - serious burns
_______________________________
When using this product do not get into eyes
_______________________________
Stop use and ask a doctor - if condition worsens
- symptoms last more than 7 days or clear up and occur again within a few days
Keep out of reach of children. If swallowed get
medical help or contact a Poison Control Center
right away.

Directions
- apply as needed.
_______________________________
Other information
- Store at 20 degrees to 25 degrees C (68 degrees to 77 degrees F)

Inactive Ingredients ceresin, lanolin alcohol, mineral oil